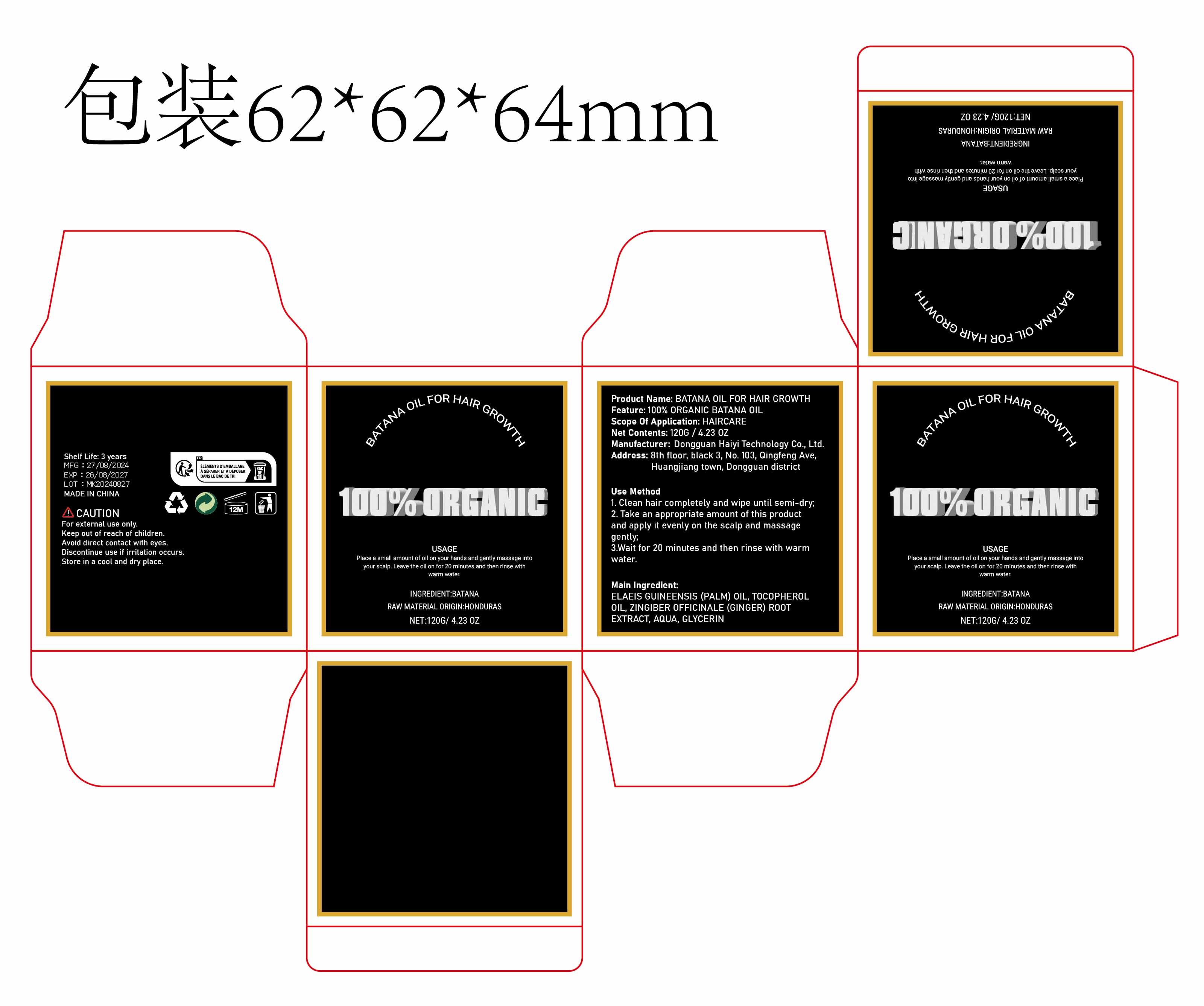 DRUG LABEL: BATANA Oil
NDC: 84732-034 | Form: PASTE
Manufacturer: Dongguan Haiyi Technology Co.,Ltd.
Category: otc | Type: HUMAN OTC DRUG LABEL
Date: 20241008

ACTIVE INGREDIENTS: PALM OIL 1 mg/100 g
INACTIVE INGREDIENTS: TOCOPHEROL; WATER; GINGER; GLYCERIN

Active ingredient

ELAEIS GUINEENSIS (PALM) OIL

Inactive ingredient

TOCOPHEROL OIL, ZINGIBER OFFICINALE (GINGER) ROOT EXTRACT, AQUA, GLYCERIN

Purpose section

Deeply moisturizes hair and improves texture

Warning

For external use only.

Keep out of reach of children.

Avoid direct contact with eyes,

Discontinue use if irritation occurs,

Store in a cool and dry place.

stop use

This product may cause allergic reactions in asmall number of people.
lf youexperience any discomfort,please stop using it immediately.

not use

Not suitable for use by children, pregnantor breast feeding people.

OUT OF CHILDREN

KEEP THE PRODUCT OUT OF REACH OF CHILDREN to

HOW TO USE

1. Clean hair completely and wipe until semi-dry;

2.Take an appropriate amount of this productand apply it evenly on the scalp and massage gently;

3.Wait for 20 minutes and then rinse with warm water.

Dosage

take an appropriateamount,Use 2-3 times a week